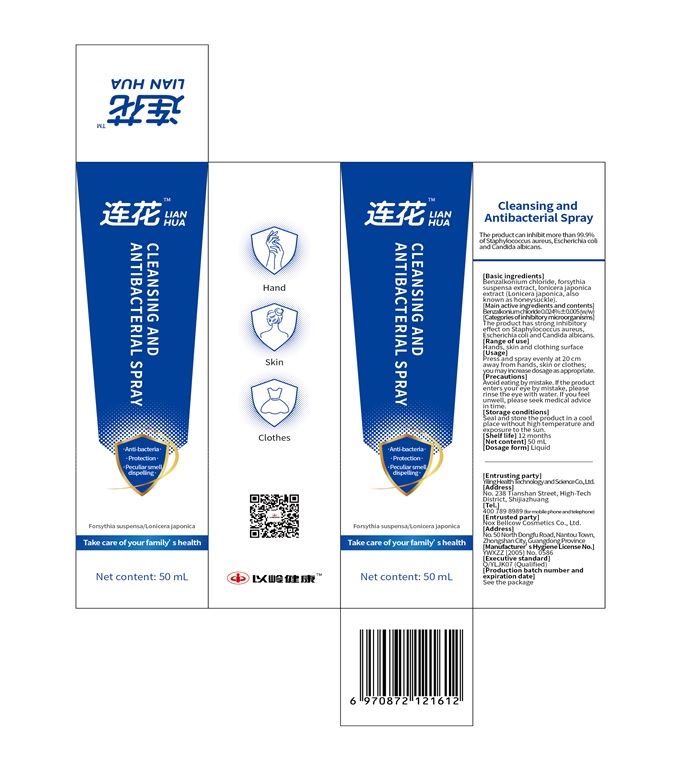 DRUG LABEL: Cleansing and Antibacterial
NDC: 80945-101 | Form: LIQUID
Manufacturer: Yiling Health Science & Technology Co. Ltd.
Category: otc | Type: HUMAN OTC DRUG LABEL
Date: 20201028

ACTIVE INGREDIENTS: BENZALKONIUM CHLORIDE 0.24 mg/1 mL
INACTIVE INGREDIENTS: FORSYTHIA SUSPENSA FRUIT; LONICERA JAPONICA FLOWER; WATER

Cleansing and Antibacterial

Cleansing and Antibacterial

Active Ingredient(s)

Benzalkonium chloride 0.24mg/mL. Purpose: Antiseptic

Purpose

Antiseptic, Cleansing and Antibacterial

Use

Cleansing and Antibacterial to help reduce bacteria that potentially can cause disease. For use when soap and water are not available.

Warnings

For external use only. Flammable. Keep away from heat or flame

Do not use

- in children less than 2 months of age
- on open skin wounds

When using this product keep out of eyes, ears, and mouth. In case of contact with eyes, rinse eyes thoroughly with water.
Stop use and ask a doctor if irritation or rash occurs. These may be signs of a serious condition.
Keep out of reach of children. If swallowed, get medical help or contact a Poison Control Center right away.

Stop use and ask a doctor if irritation or rash occurs. These may be signs of a serious condition.

Keep out of reach of children. If swallowed, get medical help or contact a Poison Control Center right away.

Directions

- Press and spray evenly at 20cm way from hangds, skin or clothes; you may increase dosage as appropriate.
- Supervise children under 6 years of age when using this product to avoid swallowing.

Other information

- Store between 15-30C (59-86F)
- Avoid freezing and excessive heat above 40C (104F)

Inactive ingredients

forsythia suspensa fruit, lonicera japonica flower, purified water USP